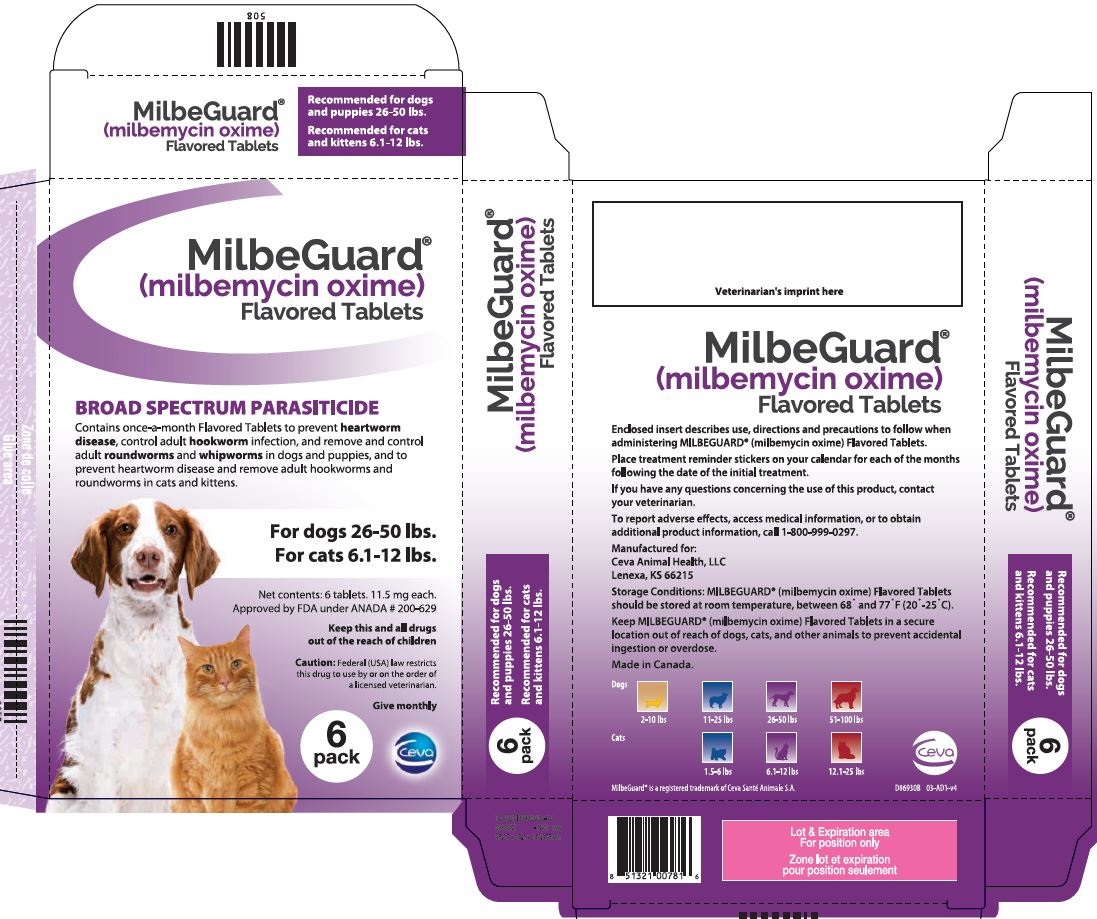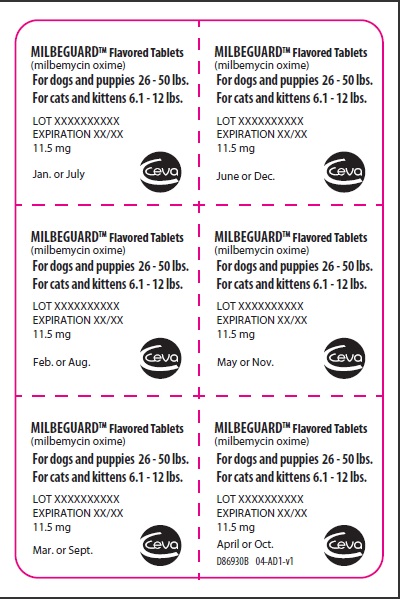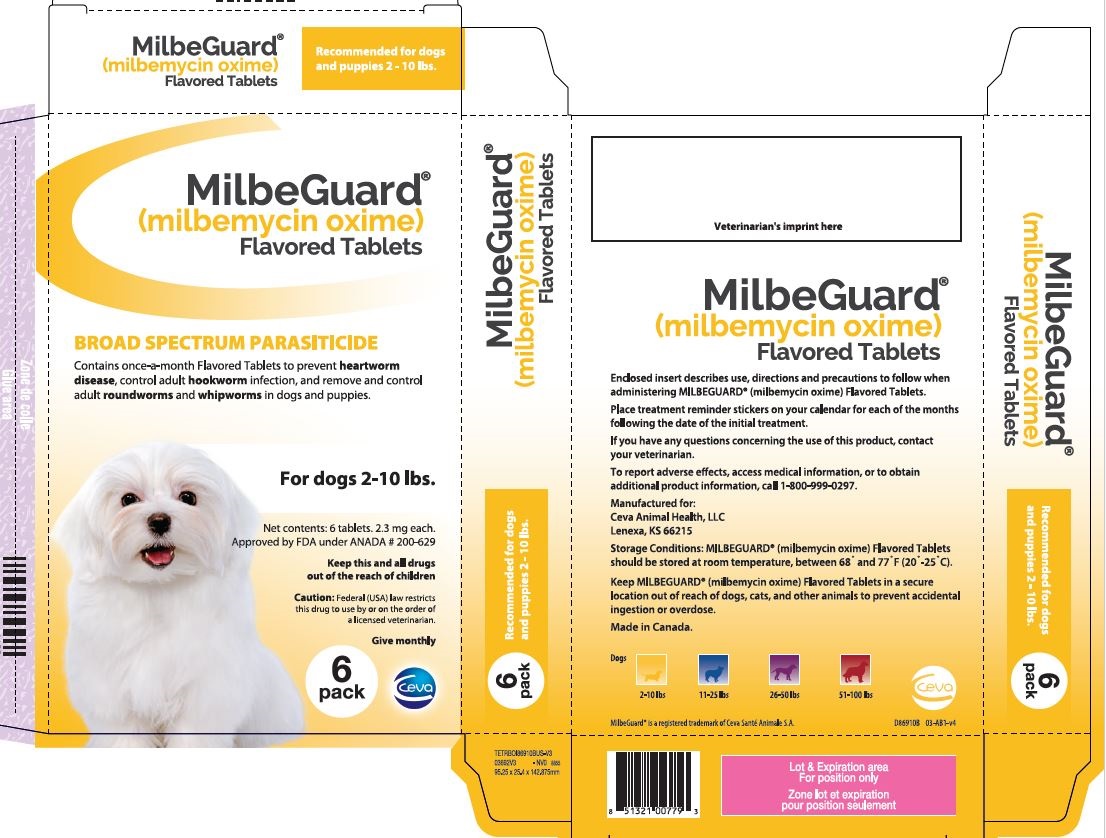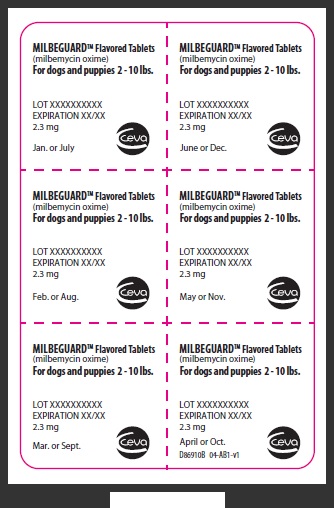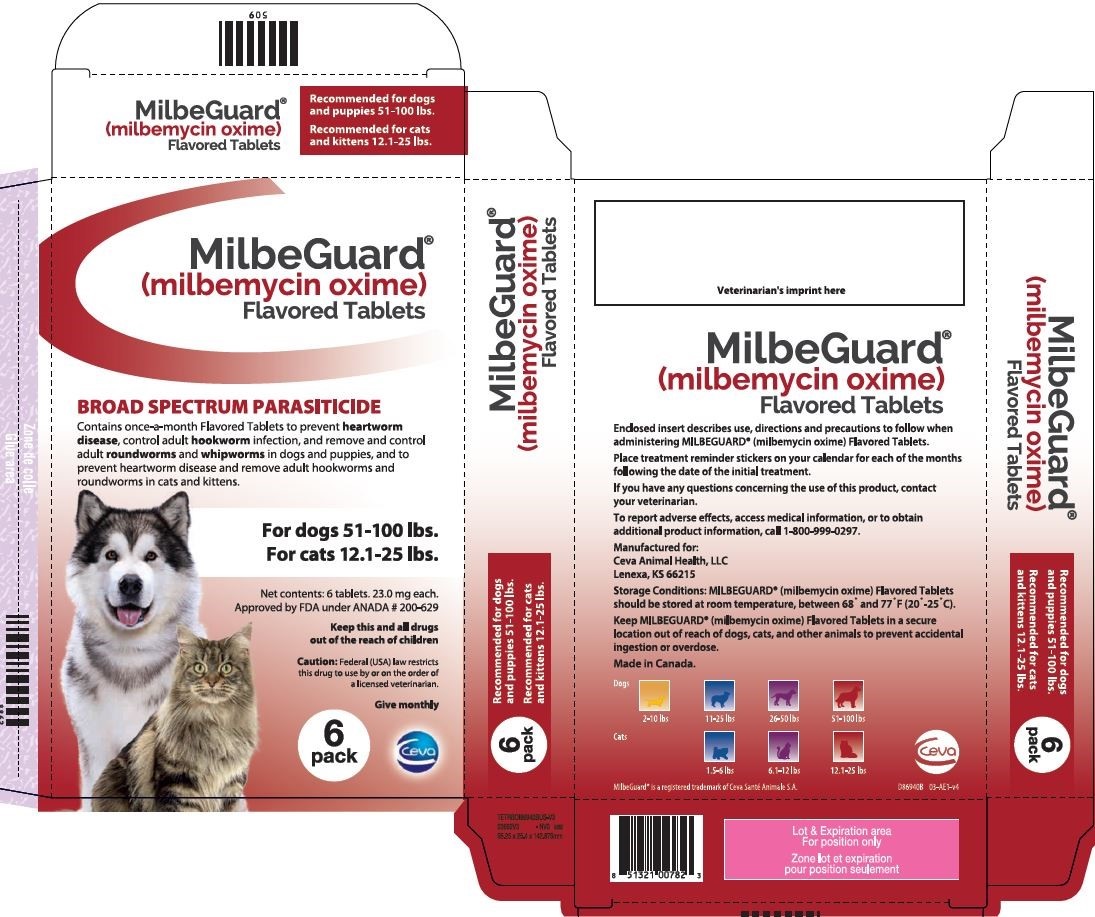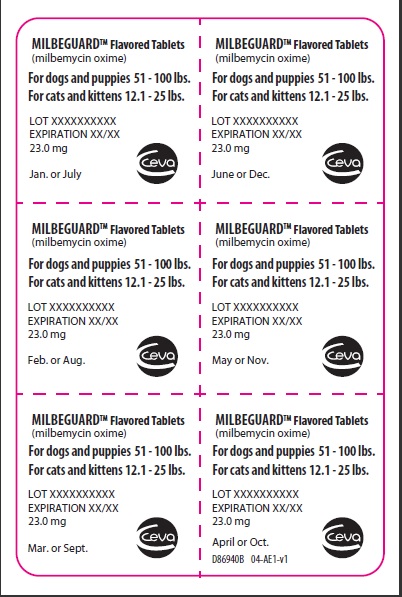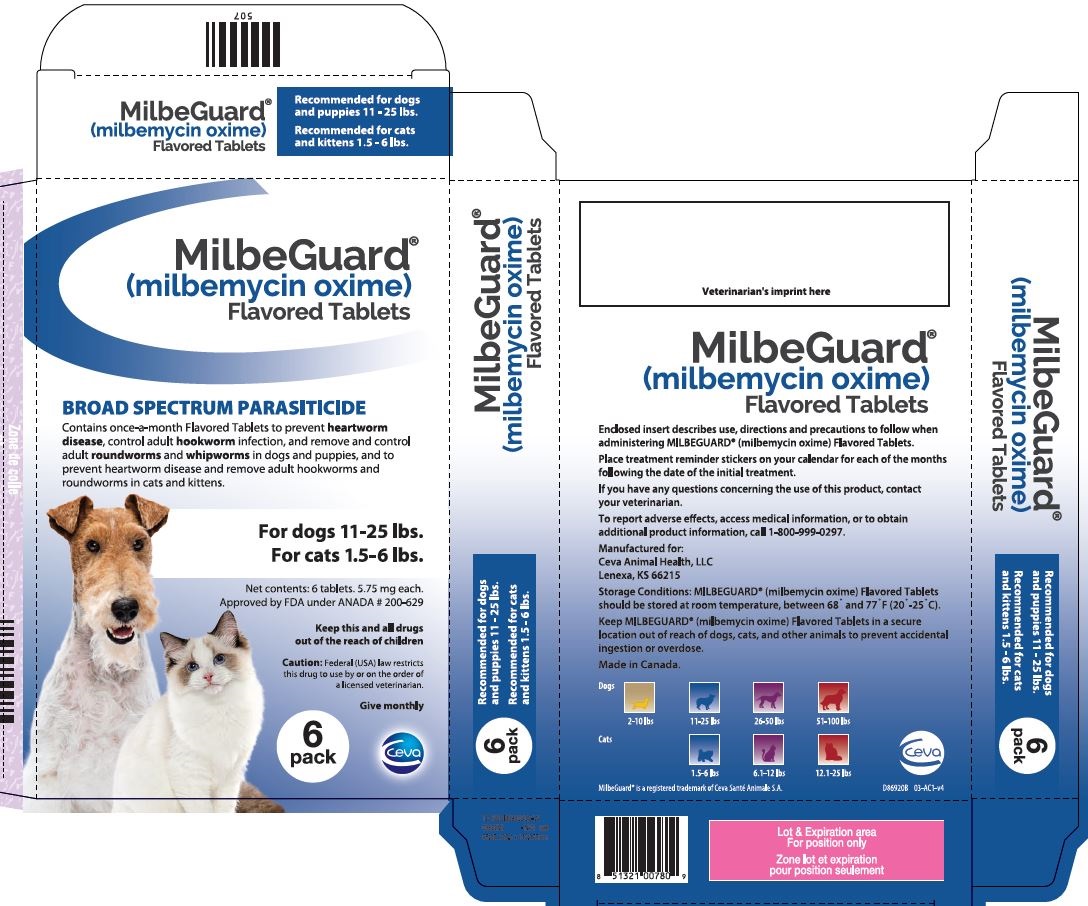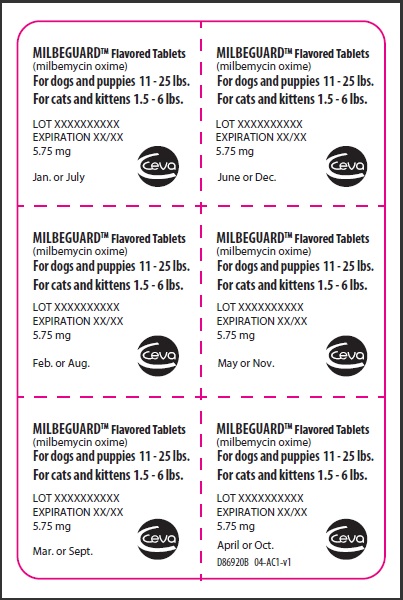 DRUG LABEL: MILBEGUARD
NDC: 13744-510 | Form: TABLET
Manufacturer: Ceva Sante Animale
Category: animal | Type: PRESCRIPTION ANIMAL DRUG LABEL
Date: 20241213

ACTIVE INGREDIENTS: MILBEMYCIN OXIME 2.3 mg/1 1

MILBEGUARD® (milbemycin oxime) Flavored Tablets

MilbeGuard®

(milbemycin oxime)

Flavored Tablets

INFORMATION FOR DOSING DOGS

The once-a-month tablet that prevents heartworm disease, controls adult hookworm, and removes and controls adult roundworm and whipworm infections in dogs and puppies.

Caution: Federal (USA) law restricts this drug to use by or on the order of a licensed veterinarian.
Keep this and all drugs out of the reach of children.

DESCRIPTION

Description: MILBEGUARD® (milbemycin oxime) Flavored Tablets are available in four tablet sizes in color-coded packages for oral administration to dogs and puppies. Each tablet is formulated to provide a minimum of 0.23 mg/lb (0.5 mg/kg) body weight of milbemycin oxime. Milbemycin oxime consists of the oxime derivatives of 5-didehydromilbemycins in the ratio of approximately 80% A4 (C32H45NO7, MW 555.71) and 20% A3 (C31H43NO7, MW 541.68).

Package Color | Milbemycin oxime tablet
Yellow | 2.3 mg*
Blue | 5.75 mg
Purple | 11.5 mg
Red | 23.0 mg

*for dogs only

INDICATIONS AND USAGE

Indications: MILBEGUARD® Flavored Tablets are indicated for use in the prevention of heartworm disease caused by Dirofilaria immitis, the control of adult Ancylostoma caninum (hookworm), and the removal and control of adult Toxocara canis and Toxascaris leonina (roundworms) and Trichuris vulpis (whipworm) infections in dogs and in puppies four weeks of age or greater and two pounds body weight or greater.

DOSAGE AND ADMINISTRATION

Dosage: MILBEGUARD® Flavored Tablets are given orally, once a month, at the recommended minimum dosage rate of 0.23 mg milbemycin oxime per pound of body weight (0.5 mg/kg).

Recommended Dosage Schedule for Dogs
Body Weight | MILBEGUARD® Flavored Tablets
2-10 lbs. | One tablet (2.3 mg)
11-25 lbs. | One tablet (5.75 mg)
26-50 lbs. | One tablet (11.5 mg)
51-100 lbs. | One tablet (23.0 mg)

Dogs over 100 Ibs. are provided the appropriate combination of tablets.

Administration: MILBEGUARD® Flavored Tablets are dual-purpose and may be offered in food or administered as other tablet medications. Watch the dog closely following dosing to be sure the entire dose has been consumed. If it is not entirely consumed, redose once with the full
recommended dose as soon as possible.

MILBEGUARD® Flavored Tablets must be administered monthly, preferably on the same date each month. The first dose should be administered within one month of the dogs first exposure to mosquitoes and monthly thereafter until the end of the mosquito season. If a dose is missed and a 30-day interval between dosing is exceeded, administer MILBEGUARD® Flavored Tablets immediately and resume the monthly dosing schedule.

If MILBEGUARD® Flavored Tablets replaces diethylcarbamazine (DEC) for heartworm prevention, the first dose must be given within 30 days after the last dose of DEC.

PRECAUTIONS

Precautions: Do not use in puppies less than four weeks of age or less than two pounds of body weight. Prior to initiation of the MILBEGUARD® Flavored Tablets treatment program, dogs should be tested for existing heartworm infections. Infected dogs should be treated to remove adult
heartworms and microfilariae prior to initiating treatment with MILBEGUARD® Flavored Tablets. Mild, transient hypersensitivity reactions manifested as labored respiration, vomiting, salivation and lethargy, have been noted in some treated dogs carrying a high number of circulating microfilariae. These reactions are presumably caused by release of protein from dead or dying microfilariae.

ADVERSE REACTIONS

Adverse Reactions: The following adverse reactions have been reported following the use of MILBEGUARD® Flavored Tablets: Depression/lethargy, vomiting, ataxia, anorexia, diarrhea, convulsions, weakness and hypersalivation.

SUMMARY OF SAFETY AND EFFECTIVENESS

Efficacy: MILBEGUARD® Flavored Tablets eliminate the tissue stage of heartworm larvae and the adult stage of hookworm (Ancylostoma caninum), roundworms (Toxocara canis, Toxascaris leonina) and whipworm (Trichuris vulpis) infestations when administered orally according to the recommended dosage schedule.The anthelmintic activity of milbemycin oxime is believed to be a result of interference with invertebrate neurotransmission.

Safety: Milbemycin oxime has been tested safely in over 75 different breeds of dogs, including collies, pregnant females, breeding males and females, and puppies over two weeks of age. In well-controlled clinical field studies, 786 dogs completed treatment with milbemycin oxime. Milbemycin oxime was used safely in animals receiving frequently used veterinary products such as vaccines, anthelmintics, antibiotics, steroids, flea collars, shampoos and dips.

Two studies in heartworm-infected dogs were conducted which demonstrated mild, transient hypersensitivity reactions in treated dogs with high microfilaremia counts (see Precautions for reactions observed). Safety studies in pregnant dogs demonstrated that high doses (1.5 mg/kg =3X) of milbemycin oxime given in an exaggerated dosing regimen (daily from mating through weaning), resulted in measurable concentrations of the drug in milk. Puppies nursing these females which received exaggerated dosing regimens demonstrated milbemycin-related effects. These effects were directly attributable to the exaggerated experimental dosing regimen. The product is normally intended for once-a-month administration only. Subsequent studies included using 3X daily from mating to one week before weaning and demonstrated no effects on the pregnant females or their litters. A second study where pregnant females were dosed once at 3X the monthly use rate either before, on the day of or shortly after whelping resulted in no effects on the puppies.

Some nursing puppies, at 2, 4, and 6 weeks of age, given greatly exaggerated oral milbemycin oxime doses (9.6 mg/kg = 19X) exhibited signs typified by tremors, vocalization and ataxia. These effects were all transient and puppies returned to normal within 24 to 48 hours. No effects were observed in puppies given the recommended dose of milbemycin oxime (0.5 mg/kg). This product has not been tested in dogs less than 1 kg weight.

A rising-dose safety study conducted in rough-coated collies, manifested a clinical reaction consisting of ataxia, pyrexia and periodic recumbency, in one of fourteen dogs treated with milbemycin oxime at 12.5 mg/kg (25X monthly use rate). Prior to receiving the 12.5 mg/kg dose (25X monthly use rate) on day 56 of the study, all animals had undergone an exaggerated dosing regimen consisting of 2.5 mg/kg milbemycin oxime (5X monthly use rate) on day 0, followed by 5.0 mg/kg (10X monthly use rate) on day 14 and 10.0 mg/kg (20X monthly use rate) on day 32. No
adverse reactions were observed in any of the collies treated with this regimen up through the 10.0 mg/kg (20X monthly use rate) dose.

HOW SUPPLIED

How supplied: MILBEGUARD® Flavored Tablets are available in four tablet sizes (see Dosage section), formulated according to the weight of the dog. Each tablet size is available in color-coded packages of 6 tablets each, which are packaged 10 per display carton.

STORAGE AND HANDLING

Storage conditions: MILBEGUARD® Flavored Tablets should be stored at room temperature, between 68° and 77°F (20-25°C).

Keep MILBEGUARD® (milbemycin oxime) Flavored Tablets in a secure location out of reach of dogs, cats, and other animals to prevent accidental ingestion or overdose.

Manufactured for:
Ceva Animal Health, LLC
Lenexa, KS 66215

Made in Canada.

Approved by FDA under ANADA #200-629

MilbeGuard®

(milbemycin oxime)

Flavored Tablets

INFORMATION FOR DOSING CATS

The once-a-month tablet that prevents heartworm disease and removes adult roundworms and hookworms in cats and kittens.

Caution: Federal (USA) law restricts this drug to use by or on the order of a licensed veterinarian.
Keep this and all drugs out of the reach of children.

DESCRIPTION

Description: MILBEGUARD® (milbemycin oxime) Flavored Tablets for Cats are available in three tablet sizes in color-coded packages for oral administration to cats and kittens. Each tablet is formulated to provide a minimum of 0.9 mg/lb (2.0 mg/kg) body weight of milbemycin oxime. Milbemycin oxime consists of the oxime derivatives of 5-didehydromilbemycins in the ratio of approximately 80% A4 (C32H45NO7, MW 555.71) and 20% A3 (C31H43NO7, MW 541.68).

Package Color | Milbemycin oxime tablet
Blue | 5.75 mg
Purple | 11.5 mg
Red | 23.0 mg

INDICATIONS AND USAGE

Indications: MILBEGUARD® Flavored Tablets for Cats are indicated for use in the prevention of heartworm disease caused by Dirofilaria immitis, and the removal of adult Ancylostoma tubaeforme (hookworm) and Toxocara cati (roundworm) in cats and kittens six weeks of age or greater and 1.5 lbs. body weight or greater.

DOSAGE AND ADMINISTRATION

Dosage: MILBEGUARD® Flavored Tablets fort Cats are given orally, once a month, at the recommended minimum dosage rate of 0.9 mg milbemycin oxime per pound of body weight (2.0mg/kg).

Recommended Dosage Schedule for Cats
Body Weight | MILBEGUARD Flavored Tablets
1.5-6 lbs. | One tablet (5.75 mg)
6.1-12 lbs. | One tablet (11.5 mg)
12.1-25 lbs. | One tablet (23.0 mg)

Administration: MILBEGUARD® Flavored Tablets for Cats may be offered in food or administered as other tablet medications. The tablets can be broken for ease of administration. Watch the cat closely following dosing to be sure the entire dose has been consumed. If it is not entirely consumed, redose once with the full recommended dose as soon as possible.

MILBEGUARD® Flavored Tablets for Cats must be administered monthly, preferably on the same date each month. The first dose should be administered within one month of the cats first exposure to mosquitoes and monthly thereafter until the end of the mosquito season. If a dose is missed and a 30-day interval between dosing is exceeded, administer MILBEGUARD® Flavored Tablets for Cats immediately and resume the monthly dosing schedule. It is recommended that cats be tested for existing heartworm infection prior to starting treatment with MILBEGUARD® Flavored Tablets for Cats (See Precautions).

PRECAUTIONS

Precautions: Do not use in kittens less than six weeks of age or less than 1.5 lbs. body weight. Safety in heartworm positive cats has not been established. Safety in breeding, pregnant, and lactating queens and breeding toms has not been established.

SUMMARY OF SAFETY AND EFFECTIVENESS

Efficacy: MILBEGUARD® Flavored Tablets for Cats eliminate the tissue stage of heartworm larvae and hookworm (Ancylostoma tubaeforme) and roundworm (Toxocara cati) infections when administered orally according to the recommended dosage schedule. The anthelmintic activity of milbemycin oxime is believed to be a result of interference with invertebrate neurotransmission.

Safety: Milbemycin oxime has been tested safely in over 8 different breeds of cats. In well-controlled clinical field studies 141 cats completed treatment with milbemycin oxime. Milbemycin oxime was used safely in animals receiving frequently used veterinary products such as vaccines, anthelmintics, anesthetics, antibiotics, steroids, flea collars, shampoos and dips.

Safety studies were conducted in young cats and kittens and doses of 1X, 3X and 5X the minimum recommended dose of 2.0 mg/kg demonstrated no drug- related effects. Tolerability studies at exaggerated doses of 10X also demonstrated no drug-related adverse effects in kittens and young adult cats.

HOW SUPPLIED

How supplied: MILBEGUARD® Flavored Tablets for Cats are available in three tablet sizes (see Dosage section), formulated according to the weight of the cat. Each tablet size is available in color-coded packages of 6 tablets each, which are packaged 10 per display carton.

STORAGE AND HANDLING

Storage conditions: MILBEGUARD® Flavored Tablets for Cats should be stored at room temperature, between 68° and 77°F (20-25°C).

Keep MILBEGUARD® (milbemycin oxime) Flavored Tablets in a secure location out of reach of dogs, cats, and other animals to prevent accidental ingestion or overdose.

Manufactured for:
Ceva Animal Health, LLC
Lenexa, KS 66215

Made in Canada.

Approved by FDA under ANADA #200-629

PRINCIPAL DISPLAY PANEL - 2.3 mg Tablet Blister Pack

MILBEGUARD® Flavored Tablets

(milbemycin oxime)

For dogs and puppies 2-10 lbs.

LOT XXXXXXXXXX

EXPIRATION XX/XX

2.3 mg

PRINCIPAL DISPLAY PANEL - 2.3 mg Carton

MilbeGuard®

(milbemycin oxime)

Flavored Tablets

BROAD SPECTRUM PARASITICIDE

Contains once-a-month Flavored Tablets to prevent heartworm disease, control adult hookworm infeaction, and remove and control adult roundworms and whipworms in dogs and puppies.

For dogs 2-10 lbs.

Net contents: 6 tablets 2.3 mg each.

Approved by FDA under ANADA #200-629

Keep this and all drugs out of the reach of children.

Caution: Federal (USA) law restricts this drug to use by or on the order of a licensed veterinarian.
Keep this and all drugs out of the reach of children.

Give monthly

6 pack

PRINCIPAL DISPLAY PANEL - 5.75 mg Tablet Blister Pack

MILBEGUARD® Flavored Tablets

(milbemycin oxime)

For dogs and puppies 11-25 lbs.

For cats and kittens 1.5-6 lbs.

LOT XXXXXXXXXX

EXPIRATION XX/XX

5.75 mg

PRINCIPAL DISPLAY PANEL - 5.75 mg Carton

MilbeGuard®

(milbemycin oxime)

Flavored Tablets

BROAD SPECTRUM PARASITICIDE

Contains once-a-month Flavored Tablets to prevent heartworm disease, control adult hookworm infeaction, and remove and control adult roundworms and whipworms in dogs and puppies, and to prevent heartworm disease and remove adult hookworms and roundworms in cats and kittens.

For dogs 11-25 lbs.

For cats 1.5-6lbs.

Net contents: 6 tablets 5.75 mg each.

Approved by FDA under ANADA #200-629

Keep this and all drugs out of the reach of children.

Caution: Federal (USA) law restricts this drug to use by or on the order of a licensed veterinarian.
Keep this and all drugs out of the reach of children.

Give monthly

6 pack

PRINCIPAL DISPLAY PANEL - 11.5 mg Tablet Blister Pack

MILBEGUARD® Flavored Tablets

(milbemycin oxime)

For dogs and puppies 26-50 lbs.

For cats and kittens 6.1-12 lbs.

LOT XXXXXXXXXX

EXPIRATION XX/XX

11.5 mg

PRINCIPAL DISPLAY PANEL - 11.5 mg Carton

MilbeGuard®

(milbemycin oxime)

Flavored Tablets

BROAD SPECTRUM PARASITICIDE

Contains once-a-month Flavored Tablets to prevent heartworm disease, control adult hookworm infeaction, and remove and control adult roundworms and whipworms in dogs and puppies, and to prevent heartworm disease and remove adult hookworms and roundworms in cats and kittens.

For dogs 26-50 lbs.

For cats 6.1-12 lbs.

Net contents: 6 tablets 11.5 mg each.

Approved by FDA under ANADA #200-629

Keep this and all drugs out of the reach of children.

Caution: Federal (USA) law restricts this drug to use by or on the order of a licensed veterinarian.
Keep this and all drugs out of the reach of children.

Give monthly

6 pack

PRINCIPAL DISPLAY PANEL - 23 mg Blister Pack

MILBEGUARD® Flavored Tablets

(milbemycin oxime)

For dogs and puppies 51-100 lbs.

For cats and kittens 12.1-25 lbs.

LOT XXXXXXXXXX

EXPIRATION XX/XX

23.0 mg

PRINCIPAL DISPLAY PANEL - 23 mg Carton

MilbeGuard®

(milbemycin oxime)

Flavored Tablets

BROAD SPECTRUM PARASITICIDE

Contains once-a-month Flavored Tablets to prevent heartworm disease, control adult hookworm infeaction, and remove and control adult roundworms and whipworms in dogs and puppies, and to prevent heartworm disease and remove adult hookworms and roundworms in cats and kittens.

For dogs 51-100 lbs.

For cats 12.1-25 lbs.

Net contents: 6 tablets 23.0 mg each.

Approved by FDA under ANADA #200-629

Keep this and all drugs out of the reach of children.

Caution: Federal (USA) law restricts this drug to use by or on the order of a licensed veterinarian.
Keep this and all drugs out of the reach of children.

Give monthly

6 pack